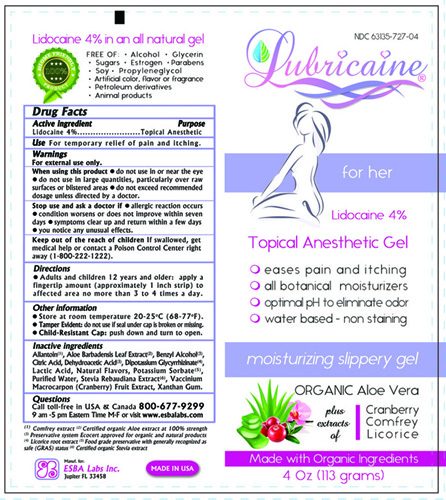 DRUG LABEL: LUBRICAINE
NDC: 63135-727 | Form: GEL
Manufacturer: ESBA LABORATORIES INC.
Category: otc | Type: HUMAN OTC DRUG LABEL
Date: 20240919

ACTIVE INGREDIENTS: LIDOCAINE 4 g/100 g
INACTIVE INGREDIENTS: LACTIC ACID, DL- 3.5 g/100 g; GLYCYRRHIZINATE DIPOTASSIUM 1 g/100 g; STEVIA REBAUDIUNA LEAF 1 g/100 g; POTASSIUM SORBATE 0.5 g/100 g; BENZYL ALCOHOL 0.54 g/100 g; DEHYDROACETIC ACID 0.06 g/100 g; VANILLA 1 g/100 g; ALOE VERA LEAF 0.5 g/100 g; ANHYDROUS CITRIC ACID 0.3 g/100 g; XANTHAN GUM 3 g/100 g; CRANBERRY 5 g/100 g; ALLANTOIN 0.4 g/100 g

LUBRICAINE

Active Ingredient

Lidocaine 4% w/w

Purpose

Topical Anesthetic

Uses

For the temporary relief of pain and itching

Warnings

For external use only.

When using this product

- do not use in or near the eye
- do not use in large quantities, particularly over raw surfaces or blistered areas
- do not exceed recommended dosage unless directed by a doctor

Stop use and ask a doctor if

- allergic reaction occurs
- condition worsens or does not improve within seven days
- symptoms clear up and return within a few days
- you notice any unusual effects

Keep out of the reach of children

If swallowed, get medical help or contact a Poison Control Center right away (1-800-222-1222)

Directions

Adults and children 12 years and older: apply a fingertip amount (approximately 1 inch strip) to affected area no more than 3 to 4 times a day

Other Information

- Store at room temperature 20-25oC (68-77oF)
- Tamper evident: do not use if foil under cap is damaged or mising.
- Child-Resistant Cap: push down and turn to open

Inactive Ingredients

Allantoin, Aloe Barbadensis Leaf Extract, Benzyl Alcohol, Citric Acid, Dehydroacetic Acid, Dipotassium Glycyrrhizinate, Lactic Acid, Natural Flavors, Potassium Sorbate, Purified Water, Stevia Rebaudiana Extract, Vaccinium Macrocarpon (Cranberry) Fruit Extract, Xanthan Gum.

Questions

Call toll-free in USA & Canada 800-677-9299 9 am to 5 pm Eastern Time M-F or visit www.esbalabs.com